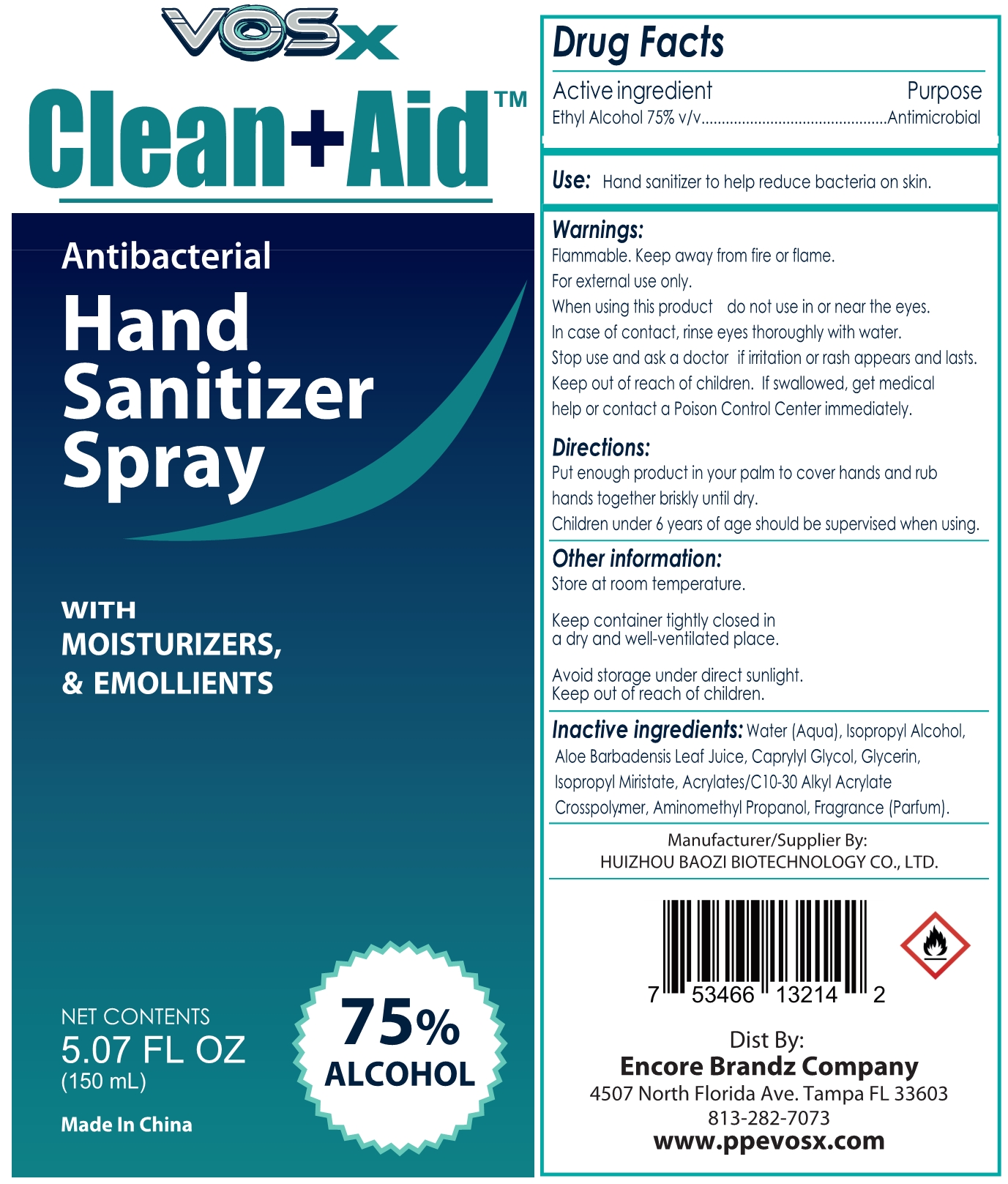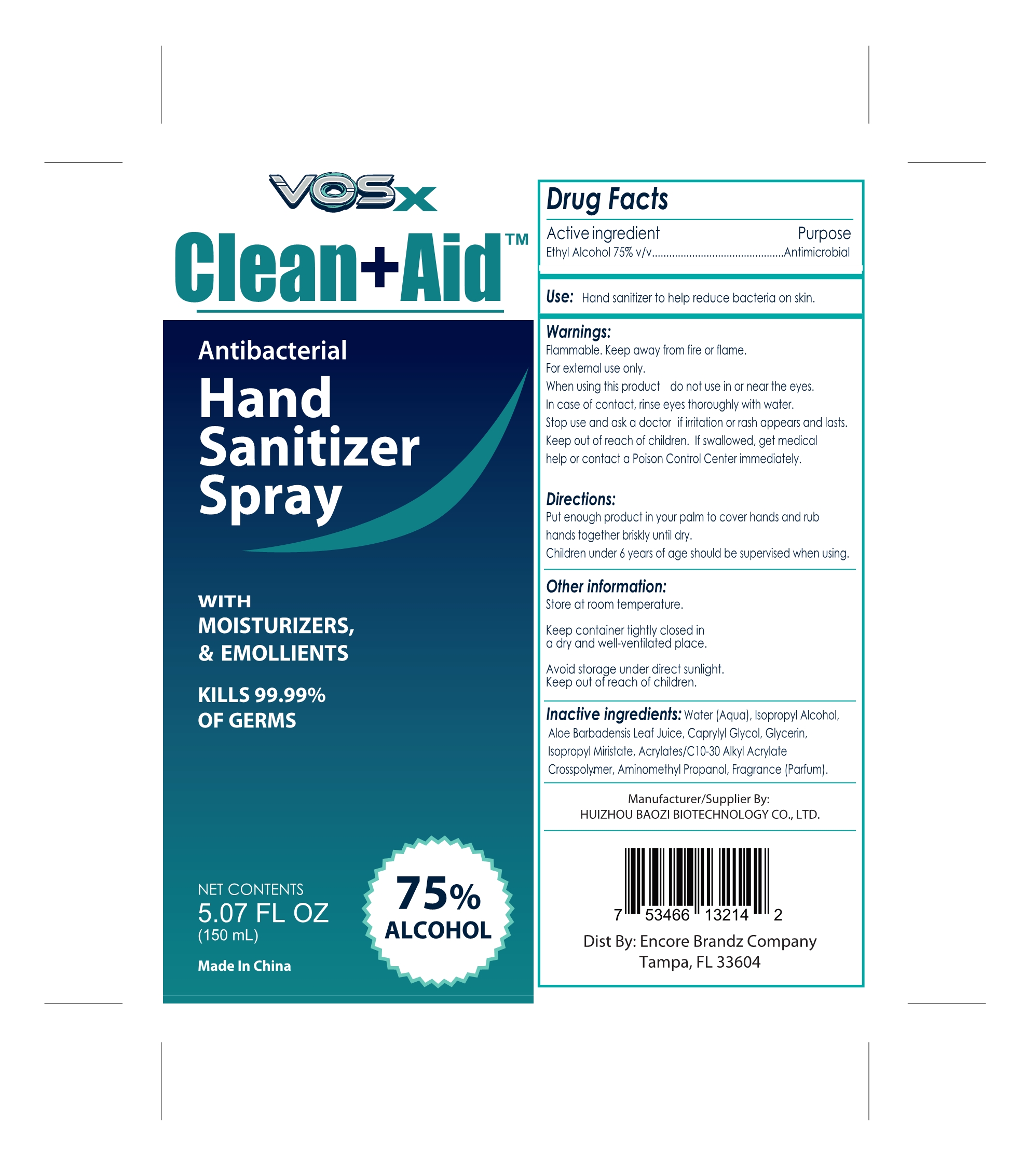 DRUG LABEL: Hand Sanitizer
NDC: 74881-005 | Form: SPRAY
Manufacturer: Huizhou Baozi Biotechnology Co., Ltd.
Category: otc | Type: HUMAN OTC DRUG LABEL
Date: 20210106

ACTIVE INGREDIENTS: ALCOHOL 75 mL/100 mL
INACTIVE INGREDIENTS: CAPRYLYL GLYCOL; ISOPROPYL MYRISTATE; GLYCERIN; ALOE VERA LEAF; CARBOMER INTERPOLYMER TYPE A (55000 CPS); WATER; ISOPROPYL ALCOHOL; 1-AMINOBUTAN-2-OL

74881-005
Hand Sanitizer

Active Ingredient

Ethyl Alcohol 75%

Purpose

Antimicrobial

Uses

Use: Hand sanitizer to help, reduce bacteria on skin

Warnings

Warnings. Flammable. Keep away from fire or flame For extend use or When using this product do not use in or near the eyes. in case of contact, rinse eyes thoroughly with water. stop use and ask a doctor if imitation or rash appears and lasts. Keep out of reach of children. I swallowed, get medical help or contact a Poison Control Center immediately

When using this product do not use in or near the eyes

When using this product do not use in or near the eyes.

stop use and ask a doctor if imitation or rash appears and lasts.

Keep out of reach of children. If swallowed, get medical help or contact a Poison Control Center immediately

Directions

Directions: Put enough product n your palm to cover hands and rub hands together brady until dry

Children 6 years of age should be supervised when using

Other information

Other information: Store at room temperature

Keep container tightly closed in a dry and well-ventilated place

Avoid storage under direct sunlight

Keep out of reach of children

Inactive ingredients

Inactive ingredients: Water (Aqua), Isopropyl Alcohol , Aloe Barbadensis Leaf Juice,

Caprylyl Glycol, Glycerin, Isopropyl Miristate, Acrylates/C10-30 Alky Acrylate Cross polymer,

Aminomethyl Propanol, Fragrance(Parfum)

Package Label - Principal Display Panel

74881-005-01 150ml

74881-005-02 150ml